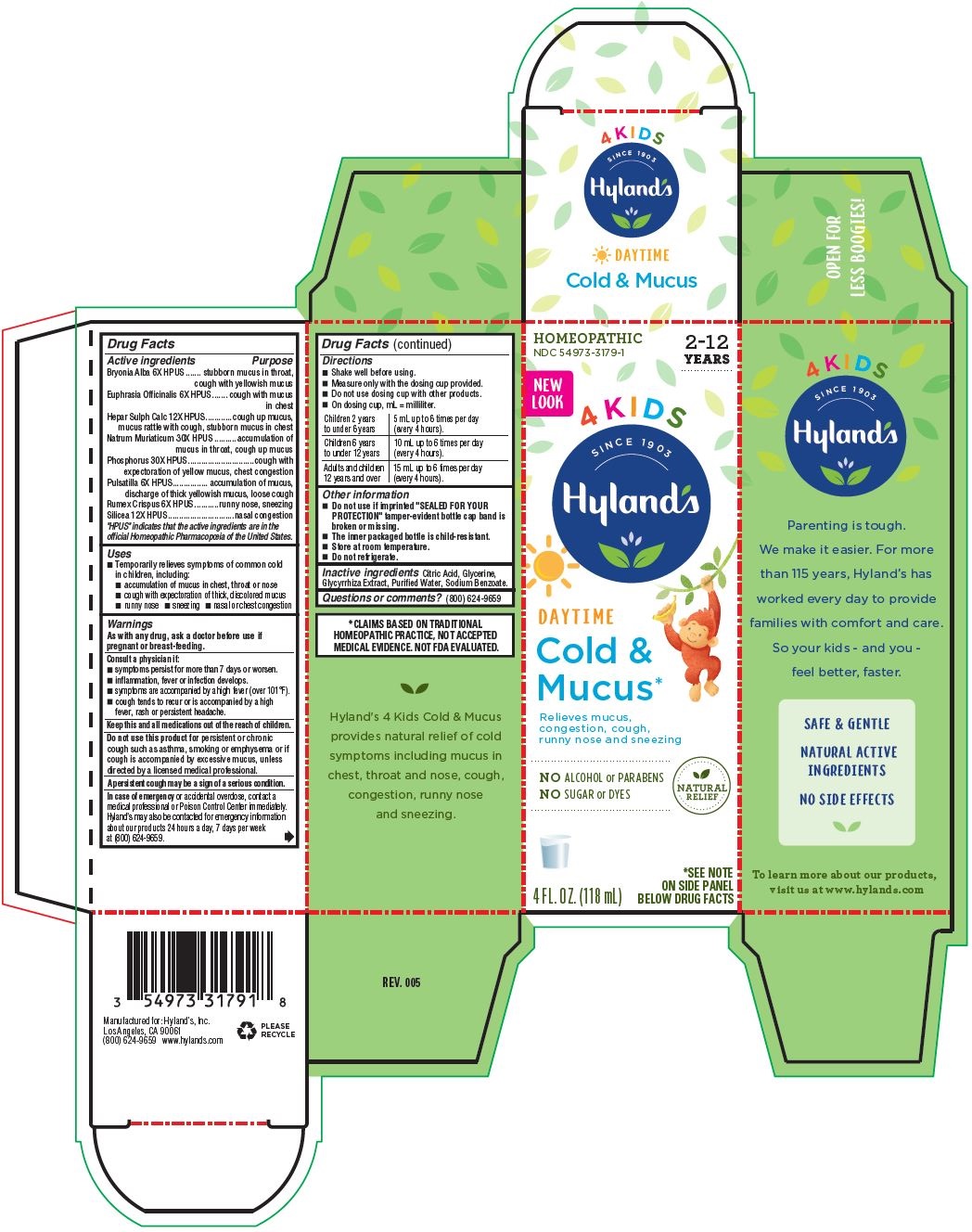 DRUG LABEL: 4 Kids Complete Cold and Mucus
NDC: 54973-3179 | Form: LIQUID
Manufacturer: Hyland's Inc.
Category: homeopathic | Type: HUMAN OTC DRUG LABEL
Date: 20221121

ACTIVE INGREDIENTS: BRYONIA ALBA ROOT 6 [hp_X]/1 mL; EUPHRASIA STRICTA 6 [hp_X]/1 mL; CALCIUM SULFIDE 12 [hp_X]/1 mL; SODIUM CHLORIDE 30 [hp_X]/1 mL; PHOSPHORUS 30 [hp_X]/1 mL; ANEMONE PULSATILLA 6 [hp_X]/1 mL; RUMEX CRISPUS ROOT 6 [hp_X]/1 mL; SILICON DIOXIDE 12 [hp_X]/1 mL
INACTIVE INGREDIENTS: CITRIC ACID MONOHYDRATE; GLYCYRRHIZA GLABRA; WATER; SODIUM BENZOATE; GLYCERIN

4 Kids Daytime Cold 'n Mucus

PURPOSE

Relieves mucus, congestion, cough, runny nose and sneezing

Drug Facts

Active ingredients | Purpose
Bryonia 6X HPUS | stubborn mucus in throat, cough with yellowish mucus
Euphrasia Officinalis 6X HPUS | cough with mucus in chest
Hepar Sulph Calc 12X HPUS | cough up mucus, mucus rattle with cough, stubborn mucus in chest
Natrum Muriaticum 30X HPUS | accumulation of mucus in throat, cough up mucus
Phosphorus 30X HPUS | cough with expectoration of yellow mucus, chest congestion
Pulsatilla 6X HPUS | accumulation of mucus, discharge of thick yellowish mucus, loose cough
Rumex Crispus 6X HPUS | runny nose, sneezing
Silicea 12X HPUS | nasal congestion

"HPUS" indicates the active ingredients are in the official Homeopathic Pharmacopœia of the United States.

Uses

■Temporarily relieves symptoms of common cold in children, including: ■ accumulation of mucus in chest, throat or nose

■ cough with expectoration of thick, discolored mucus

■ runny nose ■ sneezing ■ nasal or chest congestion

Warnings

PREGNANCY OR BREAST FEEDING

As with any drug, ask a doctor before use if pregnant or breast-feeding

ASK DOCTOR

Consult a physician if:

■ symptoms persist for more than 7 days or worsen.

■ inflammation, fever or infection develops.

■ symptoms are accompanied by a high fever (over 101°F).

■ cough tends to recur or is accompanied by a high fever, rash or persistent headache.

KEEP OUT OF REACH OF CHILDREN

Keep this and all medications out of the reach of children.

Do not use this product for persistent or chronic cough such as asthma, smoking or emphysema or if cough is accompanied by excessive mucus, unless directed by a licensed health care professional.

A persistent cough may be a sign of a serious condition.

OVERDOSAGE

In case of emergency or accidental overdose, contact a medical professional or Poison Control Center immediately. Hyland’s may also be contacted for emergency information about our products 24 hours a day, 7 days per week at (800) 624-9659.

Drug Facts (continued)

Directions

■ Measure only with the dosing cup provided

■ Do not use dosing cup with other products

■ On dosing cup, mL = milliliter, tsp = teaspoon

children 2 years to under 6 years | 5 mL up to 6 times per day (every 4 hours).
children 6 years to under 12 years | 10 mL up to 6 times per day (every 4 hours).
adults and children 12 years and over | 15 mL up to 6 times per day (every 4 hours).

Other information

■ Do not use if imprinted "SEALED FOR YOUR PROTECTION" tamper-evident bottle cap band is broken or missing.

■ The inner packaged bottle is child-resistant.

■ Store at room temperature.

■ Do not refrigerate.

Inactive ingredients

Citric Acid,Glycerine,Glycyrrhiza Extract, Purified Water, Sodium Benzoate.

Questions or comments?

(800) 624-9659

*CLAIMS BASED ON TRADITIONAL HOMEOPATHIC PRACTICE, NOT ACCEPTED MEDICAL EVIDENCE. NOT FDA EVALUATED.

RECENT MAJOR CHANGES

PDP - updated natural relief icon, applied new Hyland's logo, added 'daytime' beneath the product

name, updated illustration pants to navy blue, scrubbed packaging of spanish copy. Right Panel - updated benefits to: 'our

formulas are safe and always:' (removed mention of effective). Left Panel - updated cross sell section and HPUS

disclaimer. Drug Facts - Revised 'Consult a physician' and added 'sore throat warning' statement to match our Cold 'n

Mucus Nighttime/Cold 'n Cough SKUs (daytime/nighttime), updated tamper-evident statement to: Do not use if imprinted tamper-evident bottle band is broken or missing. Added the following statement before 'in case of emergency': The inner packaged bottle is child-resistant.

Temporarily relieves symptoms of common cold in children, including: accumulation of mucus in chest, throat or nose cough with expectoration of thick, discolored mucus runny nose  sneezing  nasal or chest congestion

Dosage and Administration Directions

Children 2 years; to under 6 years | 5 mL up to 6 times per day; (every 4 hours).
Children 6 years; to under 12 years | 10 mL up to 6 times per day; (every 4 hours).
Adults and children; 12 years and over | 15 mL up to 6 times per day; (every 4 hours).

PRINCIPAL DISPLAY PANEL - 118 mL Bottle Carton

HOMEOPATHIC

NDC 54973-3179-1

2-12

YEARS

New
Look

4 Kids

SINCE 1903
Hyland's®

DAYTIME

Cold &
Mucus *

Relieves mucus,

congestion, cough,

runny nose and sneezing

NO ALCOHOL or PARABENS

NO SUGAR or DYES

NATURAL

RELIEF

4 FL. OZ. (118 mL)

*SEE NOTE

ON SIDE PANEL

BELOW DRUG FACTS